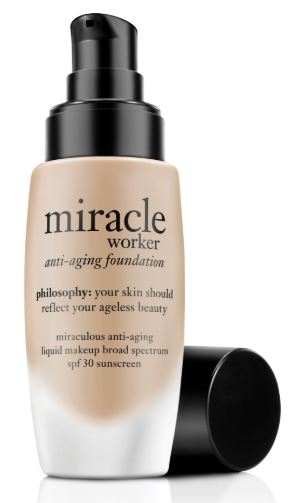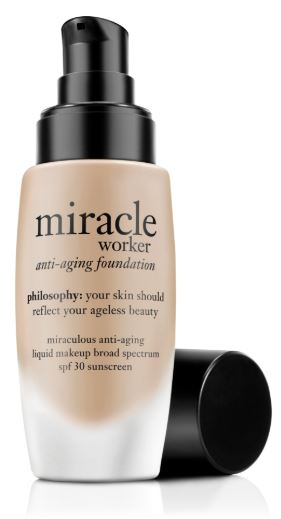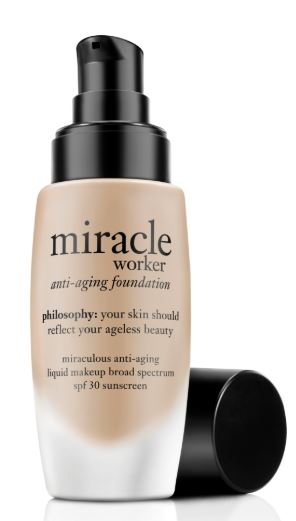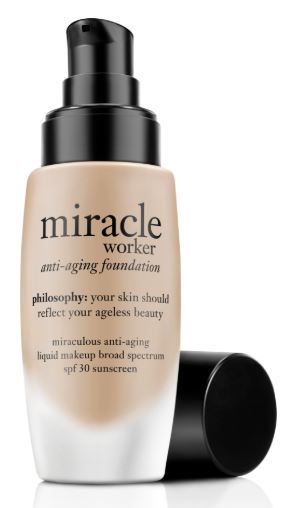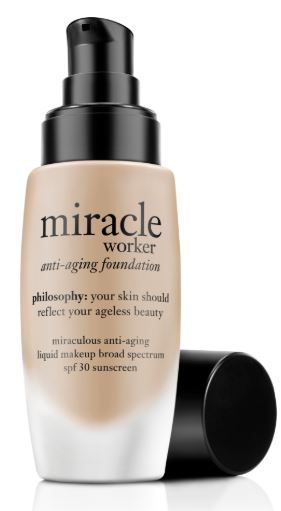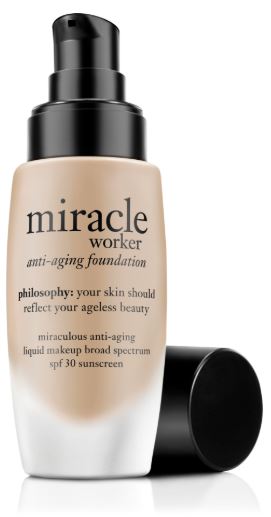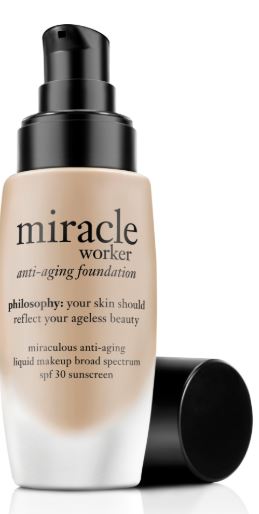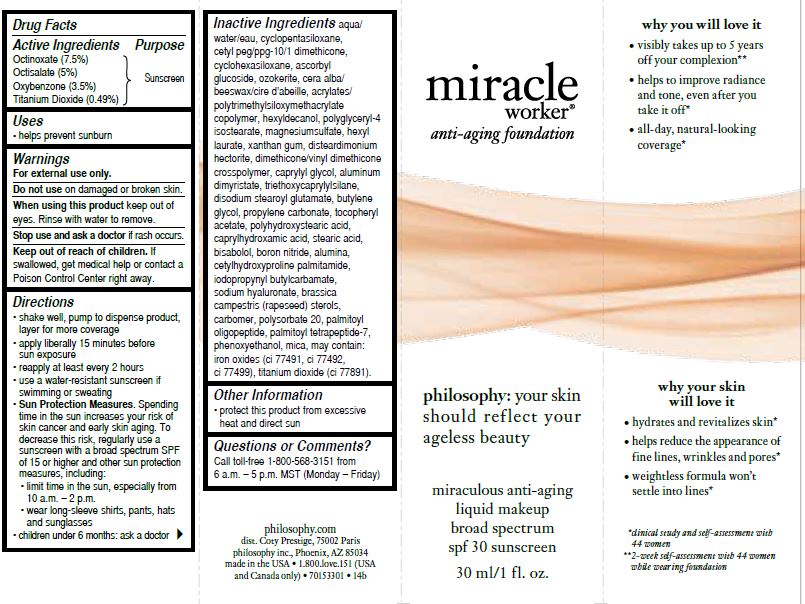 DRUG LABEL: miracle worker anti-aging foundation spf 30
NDC: 50184-1062 | Form: LIQUID
Manufacturer: Philosophy, Inc.
Category: otc | Type: HUMAN OTC DRUG LABEL
Date: 20230124

ACTIVE INGREDIENTS: OCTINOXATE 7.5 g/100 mL; OCTISALATE 5 g/100 mL; TITANIUM DIOXIDE 0.49 g/100 mL; OXYBENZONE 3.5 g/100 mL
INACTIVE INGREDIENTS: POLYSORBATE 20; WATER; DIMETHICONE; IODOPROPYNYL BUTYLCARBAMATE; MAGNESIUM SULFATE, UNSPECIFIED; XANTHAN GUM; PROPYLENE CARBONATE; CETYL PEG/PPG-10/1 DIMETHICONE (HLB 2); ASCORBYL GLUCOSIDE; BORON NITRIDE

miracle worker anti-aging foundation spf 30

Active Ingredients

Octinoxate (7.5%)

Octisalate (5%)

Oxybenzone (3.5%)

Titanium Dioxide (0.49%)

Purpose

Sunscreen

Uses

helps prevent sunburn

Warnings

For external use only.

Do not use

on damaged or broken skin.

When using this product

keep out of eyes. Rinse with water to remove.

Stop use and ask a doctor if

rash occurs.

Keep out of reach of children.

If swallowed, get medical help or contact a Poison Control Center right away.

Directions

shake well, pump to dispense product, layer for more coverage

apply liberally 15 minutes before sun exposure

reapply at least every 2 hours

use a water-resistant sunscreen if swimming or sweating

Sun Protection Measures. Spending time in the sun increases your risk of skin cancer and early skin aging. To decrease this risk, regularly use a sunscreen with a Broad Spectrum SPF value of 15 or higher and other sun protection measures including: [bullet] limit time in the sun, especially from 10 a.m.-2 p.m. [bullet] wear long-sleeved shirts, pants, hats, and sunglasses.
children under 6 months of age: ask a doctor

Inactive Ingredients

AQUA/WATER/EAU, CYCLOPENTASILOXANE, CETYL PEG/PPG-10/1 DIMETHICONE, GLYCERIN, C12-15 ALKYL BENZOATE, DIMETHICONE, CYCLOHEXASILOXANE, ASCORBYL GLUCOSIDE, OZOKERITE, CERA ALBA/BEESWAX/CIRE D'ABEILLE, ACRYLATES/POLYTRIMETHYLSILOXYMETHACRYLATE COPOLYMER, HEXYLDECANOL, PHENOXYETHANOL, POLYGLYCERYL-4 ISOSTEARATE, MAGNESIUM SULFATE, HEXYL LAURATE, XANTHAN GUM, DISTEARDIMONIUM HECTORITE, DIMETHICONE/VINYL DIMETHICONE CROSSPOLYMER, CAPRYLYL GLYCOL, ALUMINUM DIMYRISTATE, TRIETHOXYCAPRYLYLSILANE, DISODIUM STEAROYL GLUTAMATE, BUTYLENE GLYCOL, PROPYLENE CARBONATE, TOCOPHERYL ACETATE, POLYHYDROXYSTEARIC ACID, CAPRYLHYDROXAMIC ACID, STEARIC ACID, BISABOLOL, BORON NITRIDE, ALUMINA, CETYLHYDROXYPROLINE PALMITAMIDE, IODOPROPYNYL BUTYLCARBAMATE, SODIUM HYALURONATE, BRASSICA CAMPESTRIS (RAPESEED) STEROLS, CARBOMER, POLYSORBATE 20, PALMITOYL OLIGOPEPTIDE, PALMITOYL TETRAPEPTIDE- 7, IRON OXIDES (CI 77491, CI 77492, CI 77499), TITAIUM DIOXIDE (CI 77891), MICA

Other Information

protect this product in this container from excessive heat and direct sun

Questions or Comments?

Call toll-free 1-800-568-3151 from

6 a.m.-5 p.m. MST (Monday-Friday)

PACKAGE LABEL

miracle

worker

anti-aging foundation

philosophy: your skin

should reflect your

ageless beauty

miraculous anti-aging

liquid makeup

broad spectrum

spf 30 sunscreen

30 ml/1 fl. oz.